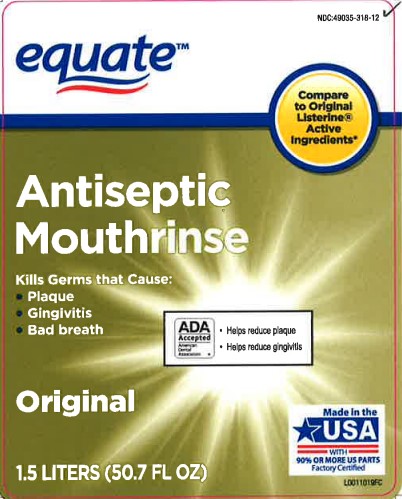 DRUG LABEL: Antiseptic
NDC: 49035-318 | Form: RINSE
Manufacturer: Walmart Inc.
Category: otc | Type: HUMAN OTC DRUG LABEL
Date: 20260227

ACTIVE INGREDIENTS: EUCALYPTOL 0.92 mg/1 mL; MENTHOL 0.42 mg/1 mL; METHYL SALICYLATE 0.6 mg/1 mL; THYMOL 0.64 mg/1 mL
INACTIVE INGREDIENTS: WATER; ALCOHOL; BENZOIC ACID; POLOXAMER 407; SODIUM BENZOATE; CARAMEL

Equate 318.003/318AI
Antiseptic Mouthrinse

TEP

Sealed with printed neckband for your protection

Active ingredients

Eucalyptol 0.092%, Menthol 0.042% Methy salicylate 0.060%, Thymol 0.064%

Purpose

Antigingivitis, Antiplaque

Use

helps control plaque that leads to gingivitis

Warnings

For this product

Do not use

If you have painful or swollen gums, pus from the gum line, loose teeth or increased spacing between the teeth. See your dentist immediately. These may be signs of periodontitis, a serious form of gum disease.

Stop use and ask a dentist if

gingivitis, bleeding, or redness persists for more than 2 weeks

Keep out of reach of children

If more than used for rinsing is accidentally swallowed, get medical help or contact a Poison Control right away.

Directions

adults and children 12 years of age and older - vigorously swish 20 ml (2/3 FL OZ or 4 teaspoonfuls) between teeth for 30 seconds then spit out; do not swallow

children under 12 years of age - consult a dentist or doctor

- this rinse is not intended to replace brushing or flossing

Other information

cold wealther may cloud this product. Its antiseptic properties are not affected. Store at room temperature (59° - 77° F)

Inactive ingredients

water, alcohol 26.9%, benzoic acid, poloxamer 407, sodium benzoate, caramel

ADVERSE REACTIONS

Satisfaction guaranteed - Or we'll replace it or give you your money back. For questions or comments or to report an undesired reaction or side effect, please call 1-888-287-1915

DISTRIBUTED BY: Wal-Mart Stores, Inc., Bentonville, AR 72716

*This product is not manufactured or distributed by Johnson & Johnson Healthcare Products, owner of the registered mark Original Listerine ®

DSP-TN-15000

DSP-MO-34

SDS-TN-15012

principal display panel

NDC 49035-318-12

equate ™

Compare to Original Listerine ® Active Ingredients*

Antiseptic Mouthrinse

Kills Germs that Cause:

Plaque
Gingivitis
Bad Breath
ADA Accepted American Dental Association

Helps reduct plaque
Helps reduce gingivits
Original

Made in the USA WITH 90% OR MORE US PARTS

Factory Certified

1.5 LITERS (50.7 FL OZ)